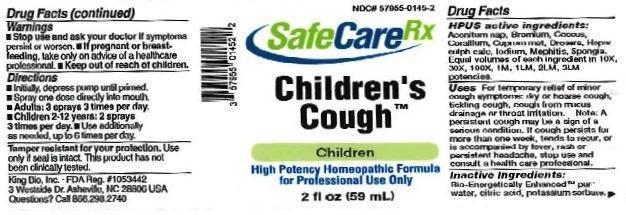 DRUG LABEL: Childrens Cough
NDC: 57955-0145 | Form: LIQUID
Manufacturer: King Bio Inc.
Category: homeopathic | Type: HUMAN OTC DRUG LABEL
Date: 20161213

ACTIVE INGREDIENTS: ACONITUM NAPELLUS 10 [hp_X]/59 mL; BROMINE 10 [hp_X]/59 mL; PROTORTONIA CACTI 10 [hp_X]/59 mL; CORALLIUM RUBRUM EXOSKELETON 10 [hp_X]/59 mL; COPPER 10 [hp_X]/59 mL; DROSERA ROTUNDIFOLIA 10 [hp_X]/59 mL; CALCIUM SULFIDE 10 [hp_X]/59 mL; IODINE 10 [hp_X]/59 mL; MEPHITIS MEPHITIS ANAL GLAND FLUID 10 [hp_X]/59 mL; SPONGIA OFFICINALIS SKELETON, ROASTED 10 [hp_X]/59 mL
INACTIVE INGREDIENTS: WATER; ANHYDROUS CITRIC ACID; POTASSIUM SORBATE

Children's Cough™

ACTIVE INGREDIENT

Drug Facts__________________________________________________________________________________________________________

HPUS active ingredients: Aconitum napellus, Bromium, Coccus cacti, Corallium rubrum, Cuprum metallicum, Drosera, Hepar sulphuris calcareum, Iodium, Mephitis mephitica, Spongia tosta. Equal volumes of each ingredient in 10X, 30X, 100X, 1M, 1LM, 2LM, 3LM potencies.

INDICATIONS AND USAGE

Uses for temporary relief of minor cough symptoms: dry or hoarse cough, tickling cough, cough from mucus drainage or throat irritation. Note: A persistent cough may be a sign of a serious condition. If cough persists for more than one week, tends to recur, or is accompanied by fever, rash or persistent headache, stop use and consult a health care professional.

Inactive Ingredients:

Bio-Energetically Enhanced™ pure water, citric acid and potassium sorbate.

Warnings

- Stop use and ask your doctor if symptoms persist or worsen.
- If pregnant or breast-feeding, take only on advice of a healthcare professional.

- Keep out of reach of children.

Directions

- Initially, depress pump until primed.
- Spray one dose directly into mouth.
- Adults: 3 sprays 3 times per day.
- Children 2-12 years: 2 sprays 3 times per day
- Use additionally as needed, up to 6 times per day.

OTHER SAFETY INFORMATION

Tamper resistant for your protection. Use only if safety seal is intact. This product has not been clinically tested.

PURPOSE

Uses for temporary relief of minor cough symptoms:

- dry or hoarse cough
- tickling cough
- cough from mucus drainage or throat irritation
- Note: A persistent cough may be a sign of a serious condition. If cough persists for more than one week, tends to recur, or is accompanied by fever, rash or persistent headache, stop use and consult a health care professional.